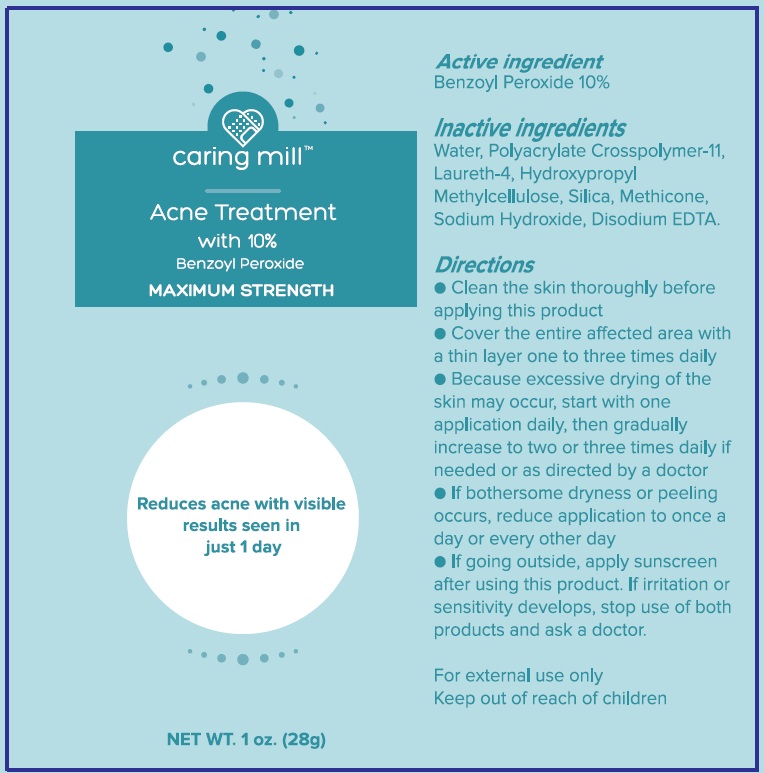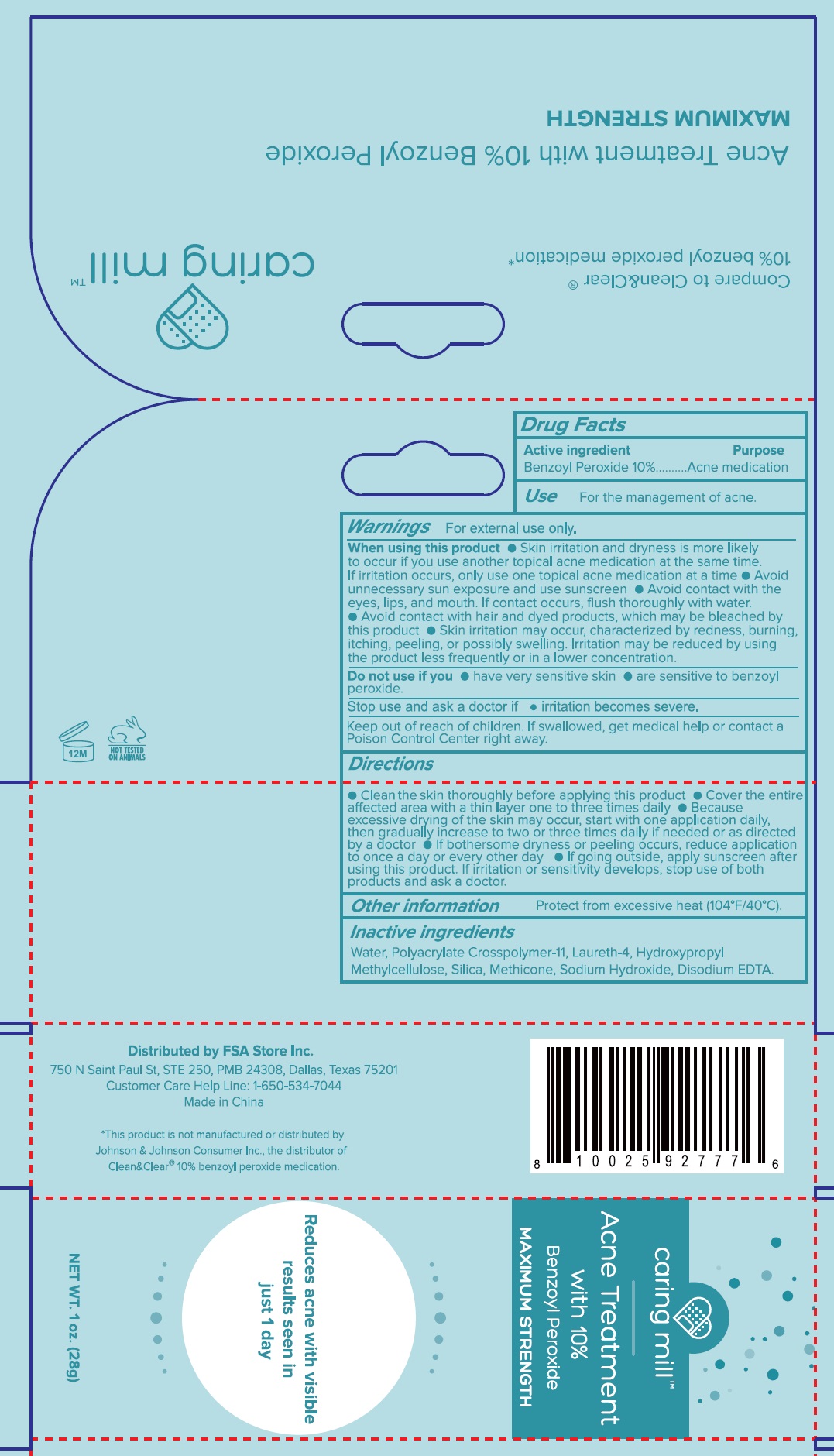 DRUG LABEL: Caring mill Acne Treatment
NDC: 81522-951 | Form: CREAM
Manufacturer: FSA Store Inc.
Category: otc | Type: HUMAN OTC DRUG LABEL
Date: 20240112

ACTIVE INGREDIENTS: BENZOYL PEROXIDE 100 mg/1 g
INACTIVE INGREDIENTS: WATER; AMMONIUM ACRYLOYL DIMETHYLTAURATE/METHACRYLATE, DIMETHYLACRYLAMIDE AND METHACRYLIC ACID COPOLYMER, PPG-3 GLYCERYL TRIACRYLATE CROSSLINKED (100000 MW); LAURETH-4; HYPROMELLOSE, UNSPECIFIED; SILICON DIOXIDE; METHICONE (20 CST); SODIUM HYDROXIDE; EDETATE DISODIUM ANHYDROUS

Caring mill Acne Treatment

Active Ingredient

Benzoyl Peroxide 10%

Purpose

Acne medication

Use

For the management of acne.

Warnings

For external use only.

When using this product

- Skin irritation and dryness is more likely to occur if you use another topical acne medication at the same timr. If irritation occurs, only use one topical acne medication at a time
- Avoid unnecessary sun exposure and use sunscreen
- Avoid contact with the eyes, lips, and mouth. If contact occurs, flush thorughly with water.
- Avoid contact with hair and dyed products, which may be bleached by this product
- Skin irritation may occur, characterized by redness, burning, itching, peeling, or possibly swelling. Irritation may be reduced by using the product less frequently or in a lower concentration.

Do not use if you

- have very sensitive skin
- are sensitive to benzoyl peroxide.

Stop use and ask a doctor if

- irritation becomes severe.

Keep out of reach of children.

If swallowed, get medical help or contact a Poison Control Center right away.

Directions

- Clean the skin thoroughly before applying this product
- Cover the entire affected area with a thin layer one to three times daily
- Because excessive drying of the skin may occur, start with one application daily, then gradually increase to two or three times daily if needed or as directed by a doctor
- If bothersome dryness or peeling occurs, reduce applicaiton to once a day or every other day
- If going outside, apply sunscreen after using this product. If irritaion or sensitivity develops, stop use of both products and ask a doctor.

Other information

Protect from excessive heat (104°F/40°C).

Inactive ingredients

Water, Polyacrylate Crosspolymer-11, Laureth-4, Hydroxypropyl Methylcellulose, Silica, Methicone, Sodium Hydroxide, Disodium EDTA.